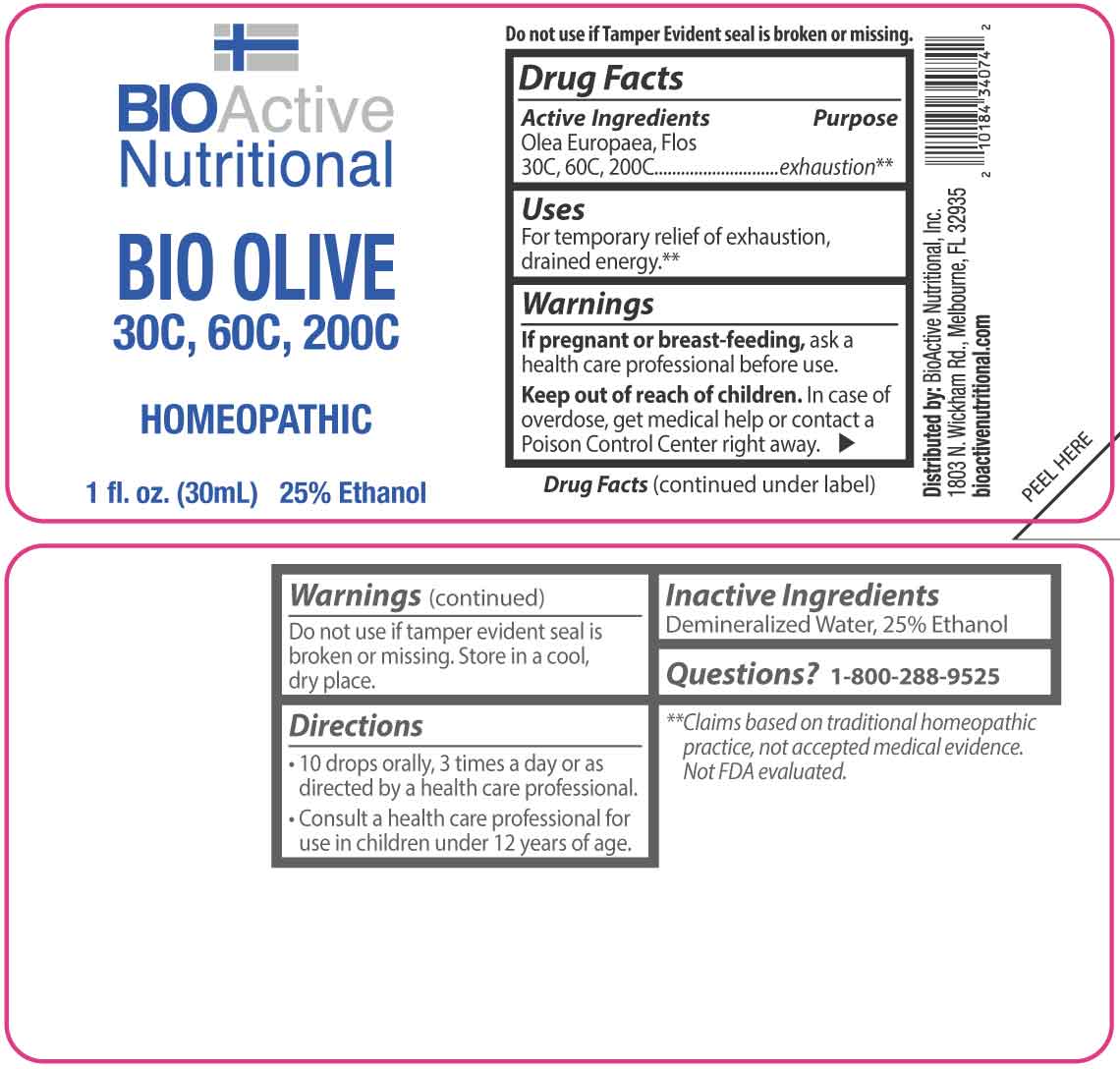 DRUG LABEL: Bio Olive 30C, 60C, 200C
NDC: 43857-0666 | Form: LIQUID
Manufacturer: BioActive Nutritional, Inc.
Category: homeopathic | Type: HUMAN OTC DRUG LABEL
Date: 20260120

ACTIVE INGREDIENTS: OLEA EUROPAEA FLOWER 30 [hp_C]/1 mL
INACTIVE INGREDIENTS: WATER; ALCOHOL

DRUG FACTS:

ACTIVE INGREDIENTS:

Olea Europaea, Flos 30C, 60C, 200C.

PURPOSE:

Olea Europaea, Flos - exhaustion**

**Claims based on traditional homeopathic practice, not accepted medical evidence. Not FDA evaluated.

USES:

For temporary relief of exhaustion, drained energy.**

**Claims based on traditional homeopathic practice, not accepted medical evidence. Not FDA evaluated.

WARNINGS:

If pregnant or breast-feeding, ask a health care professional before use.

Keep out of reach of children. In case of overdose, get medical help or contact a Poison Control Center right away.

Do not use if tamper evident seal is broken or missing.

Store in a cool, dry place.

KEEP OUT OF REACH OF CHILDREN:

In case of overdose, get medical help or contact a Poison Control Center right away.

DIRECTIONS:

• 10 drops orally, 3 times a day or as directed by a health care professional.

• Consult a health care professional for use in children under 12 years of age.

INACTIVE INGREDIENTS:

Demineralized Water, 25% Ethanol

QUESITONS:

Distributed by:
BioActive Nutritional, Inc.
1803 N. Wickham Rd.
Melbourne, FL 32935
bioactivenutritional.com

1/800-288-9525

PACKAGE LABEL DISPLAY:

BIOActive Nutritional

BIO OLIVE 30C, 60C, 200C

HOMEOPATHIC

1 fl. oz. (30mL)